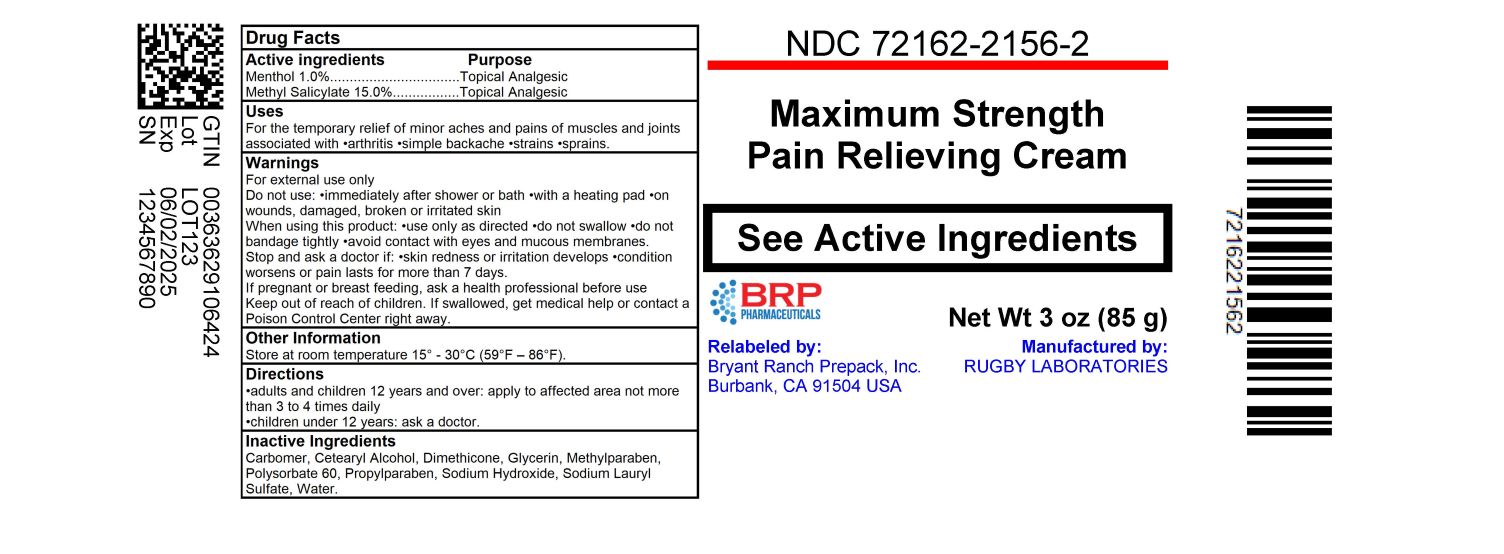 DRUG LABEL: Rugby Pain Relieving  
NDC: 72162-2156 | Form: CREAM
Manufacturer: Bryant Ranch Prepack
Category: otc | Type: HUMAN OTC DRUG LABEL
Date: 20240222

ACTIVE INGREDIENTS: MENTHOL, UNSPECIFIED FORM 10 mg/1 g; METHYL SALICYLATE 150 mg/1 g
INACTIVE INGREDIENTS: CARBOXYMETHYLCELLULOSE SODIUM, UNSPECIFIED; CETOSTEARYL ALCOHOL; DIMETHICONE; GLYCERIN; METHYLPARABEN; POLYSORBATE 60; PROPYLPARABEN; SODIUM HYDROXIDE; SODIUM LAURYL SULFATE; WATER

Rugby® Pain Relieving Cream
Topical Analgesic

Drug Facts

ACTIVE INGREDIENT

Active ingredients | Purpose
Menthol 1.0% | Topical Analgesic
Methyl Salicylate 15.0% | Topical Analgesic

Use

For the temporary relief of minor aches and pains of muscles and joints associated with

♦ arthritis
♦ simple backache
♦ strains
♦ sprains

Warnings

For external use only

Do not use

♦ immediately after shower or bath
♦ with a heating pad
♦ on wounds, damaged, broken or irritated skin

When using this product

♦ use only as directed
♦ do not swallow
♦ do not bandage tightly
♦ avoid contact with eyes and mucous membranes

Stop and ask a doctor if

♦ skin redness or irritation develops
♦ condition worsens or pain lasts for more than 7 days

PREGNANCY OR BREAST FEEDING

If pregnant or breast feeding, ask a health professional before use

Keep out of reach of children. If swallowed, get medical help or contact a Poison Control Center right away.

Directions

♦ adults and children 12 years and over: apply to affected area not more than 3 to 4 times daily
♦ children under 12 years: ask a doctor.

Other information

Store at room temperature 15° - 30°C (59°F – 86°F).

Inactive ingredients

Carbomer, Cetearyl Alcohol, Dimethicone, Glycerin, Methylparaben, Polysorbate 60, Propylparaben, Sodium Hydroxide, Sodium Lauryl Sulfate, Water

Questions or comments?

1-800-645-2158

Distributed by:
Rugby Laboratories
31778 Enterprise Drive
Livonia, MI 48150

HOW SUPPLIED

NDC: 72162-2156-2: 85 g in a TUBE

Repackaged/Relabeled by:
Bryant Ranch Prepack, Inc.
Burbank, CA 91504

PACKAGE LABEL

Pain Relieving Cream